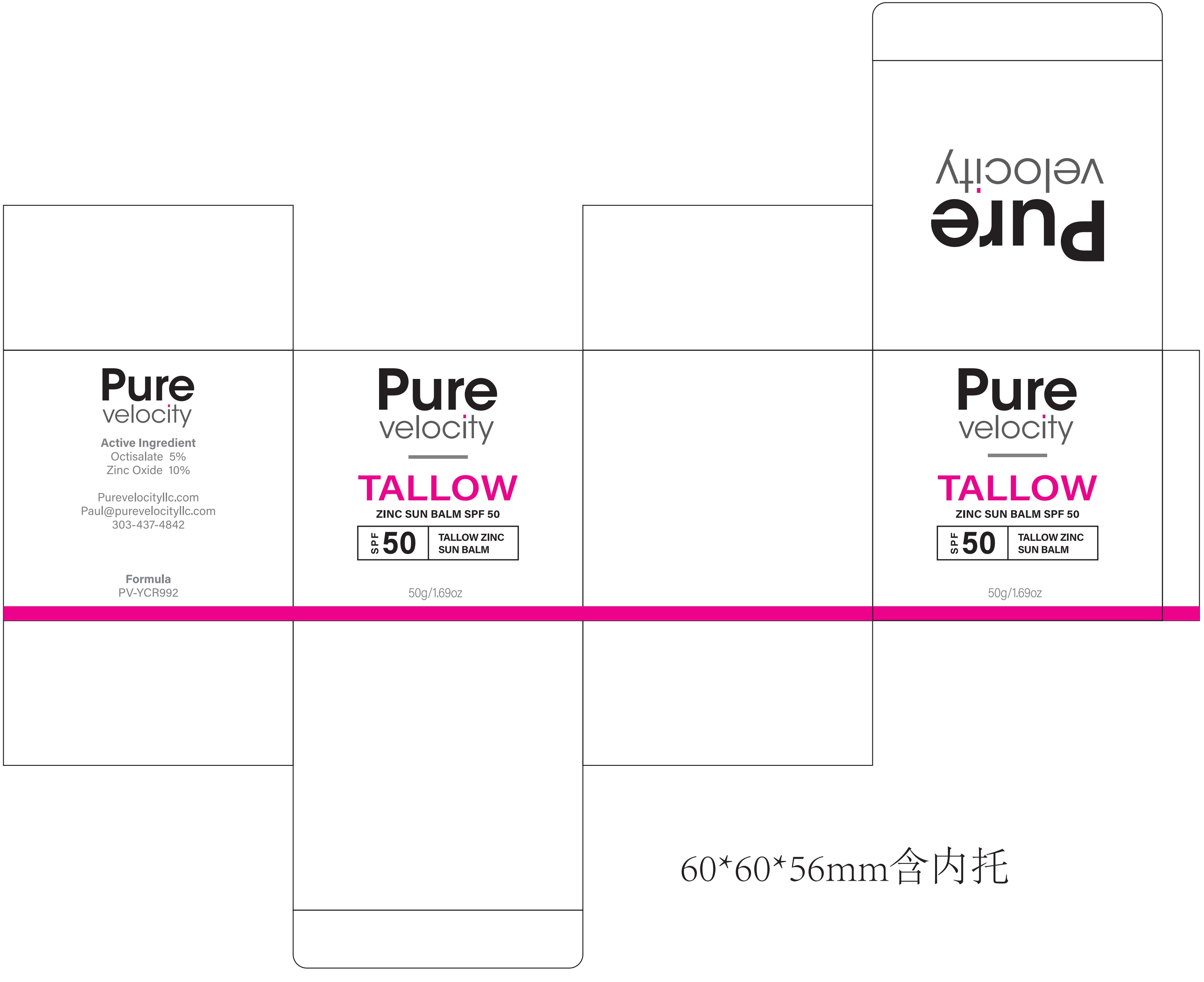 DRUG LABEL: Pure velocity TALLOW ZINC SUN BALM SPF 50
NDC: 60771-0034 | Form: CREAM
Manufacturer: Guangzhou Haishi Biological Technology Co., Ltd.
Category: otc | Type: HUMAN OTC DRUG LABEL
Date: 20250930

ACTIVE INGREDIENTS: ZINC OXIDE 5 g/100 g; ETHYLHEXYL SALICYLATE 2.5 g/100 g
INACTIVE INGREDIENTS: PARFUMIDINE; WATER; ETHYLHEXYL PALMITATE; SIMMONDSIA CHINENSIS (JOJOBA) SEED OIL; ABIES ALBA WHOLE; DIMETHICONE; SILICA DIMETHYL SILYLATE; ROSA CANINA FRUIT OIL; BISABOLOL; .ALPHA.-TOCOPHEROL ACETATE, DL-; ADEPS BOVIS; BEESWAX

Active Ingredients

ETHYLHEXYL SALICYLATE
ZINC OXIDE

Purpose

SUNSCREEN

Uses

If used as directed with other sun protection measures(see Directions)，
decreases the risk of skin cancer and early skin aging caused by the sun.

Warnings

For external use only

Stop Use

Rinse with wate to remove.
Stop use and ask doctor if rash occurs.

Do not use on damaged or broken skin.

When Using

When using this product keep out of eyes.

Keep Out Of Reach Of Children

Dosage & administration

Squeeze out an appropriate amount of Sunscreen and spread evenly on skin.

Inactive ingredients

ETHYLHEXYL PALMITATE
ADEPS BOVIS
SIMMONDSIA CHINENSIS (JOJOBA) SEED OIL
OZOKERITE
CERA ALBA
DIMETHICONE
SILICA DIMETHYL SILYLATE
TOCOPHEROL
ROSA CANINA FRUIT OIL
PARFUM
BISABOLOL
WATER